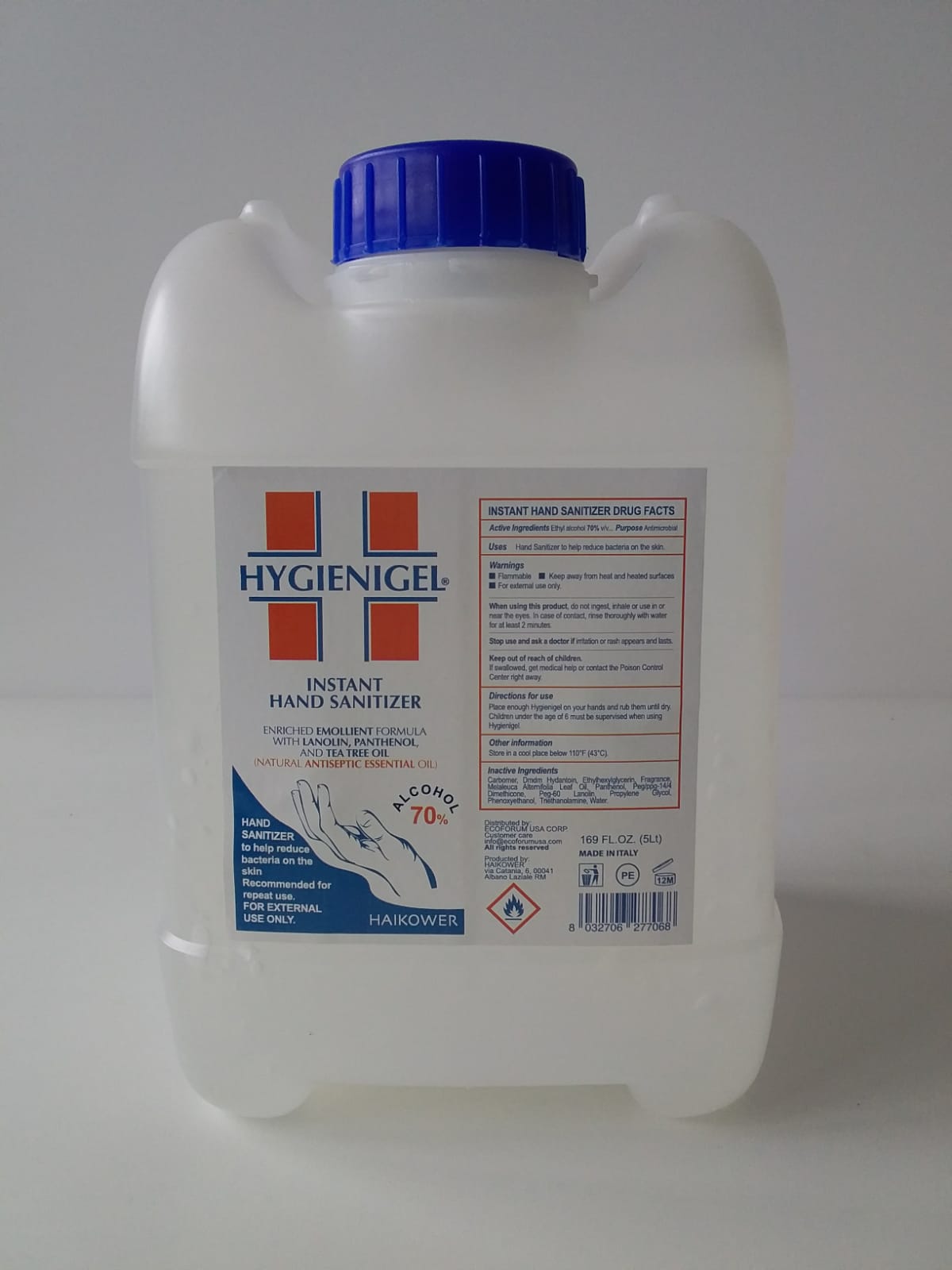 DRUG LABEL: HYGIENIGEL
NDC: 78619-200 | Form: GEL
Manufacturer: HAIKOWER S.r.l.
Category: otc | Type: HUMAN OTC DRUG LABEL
Date: 20210302

ACTIVE INGREDIENTS: ALCOHOL 70 mL/100 mL
INACTIVE INGREDIENTS: ETHYLHEXYLGLYCERIN; MELALEUCA ALTERNIFOLIA LEAF; LANOLIN; TRIETHANOLAMINE LAURATE; WATER; PHENOXYETHANOL; CARBOMER 1342; FRAGRANCE LEMON ORC2001060; PANTHENOL; PEG/PPG-14/4 DIMETHICONE; PROPYLENE GLYCOL 1-LAURATE; DMDM HYDANTOIN

Hygienigel Gel - 70%

Dosage and Admin

Place enough HYGIENIGEL on your hands and rub them until dry.

Children under 6 years of age must be supervised when using HYGIENIGEL.

Inactive ingredients

Carbomer, Dmdm Hydantoin, Ethylhexylglycerin, Fragrance, Melaleuca Alternifolia Leaf Oil, Panthenol, Peg/ppg-14/4 Dimethicone, Peg-60 Lanolin, Propylene Glycol, Phenoxyethanol, Triethanolamine, Water

Active Ingredient

Ethyl Alcohol 70% v/v

OTC - Ask Doctor

Stop use and ask a doctor if irritation or rash appears and lasts.

OTC - Do not use

When using this product, do not ingest, inhale or use in or near the eyes. In case of contact, rinse thoroughly with water for at least 2 minutes.

OTC - Keep out of children

Keep out of reach of children.

If swallowed, get medical help or contact the Poison Control Center right away.

OTC - Purpose

Uses Hand Sanitizer to help reduce bacteria on the skin

OTC - Stop use

Stop use and ask a doctor if irritation or rash appears and lasts.

Warnings

Flammable.

Keep away from flame and fire.

For external use only.

Indication and USage

Hand Sanitizer to help reduce bacteria on the skin